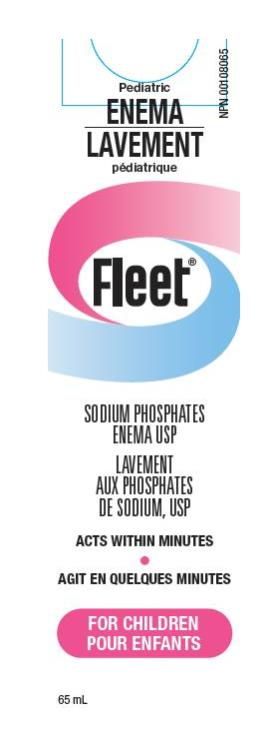 DRUG LABEL: Fleet for Children
NDC: 0132-0555 | Form: ENEMA
Manufacturer: C.B. Fleet Company, Inc.
Category: otc | Type: HUMAN OTC DRUG LABEL
Date: 20211112

ACTIVE INGREDIENTS: SODIUM PHOSPHATE, DIBASIC, HEPTAHYDRATE 3.5 g/66 mL; SODIUM PHOSPHATE, MONOBASIC 9.5 g/66 mL
INACTIVE INGREDIENTS: WATER; EDETATE DISODIUM; BENZETHONIUM CHLORIDE

Fleet Enema, Child, Canada 0132-0555-20

Active Ingredient (in each 59-mL delivered dose)

Monobasic Sodium Phosphate 9.5 g.................

Dibasic Sodium Phosphate 3.5 g......................

Purpose

Laxative / Bowel Cleanser

Laxative / Bowel Cleanser

Use

For relief of occasional constipation or bowel cleansing before rectal examinations.

Warnings

Using more than one enema in 24 hours can be harmful.

Ask a doctor before using this product if the child

- is on a sodium-restricted diet
- has kidney disease

Ask a doctor before using any laxative if the child has:

- abdominal pain, nausea, or vomiting
- a sudden change in bowel habits lasting more than 2 weeks
- already used a laxative for more than 1 week

Stop use and consult a doctor if the child has

- rectal bleeding
- no bowel movement ater the enema is given

These symptoms may indicate a serious condition.

Keep out of reach of children

In case of overdose or accidental ingestion, get medical help right away.

Other Information

Inactive Ingredients

benzalkonium chloride, disodium EDTA, purified water

Questions?

C.B. Fleet Co., Inc.

Lynchburg, VA 24502

U.S.A.

Directions

Do not use more unless directed by a doctor. See Warnings
children 5 to 11 years | One bottle or as directed by a doctor
children 2 to under 5 years | One-half bottle
children under 2 years | DO NOT USE

PRINCIPAL DISPLAY PANEL

Fleet
SODIUM PHOSPHATES
ENEMA USP
ACTS WITHIN MINUTES
FOR CHILDREN
65 ML